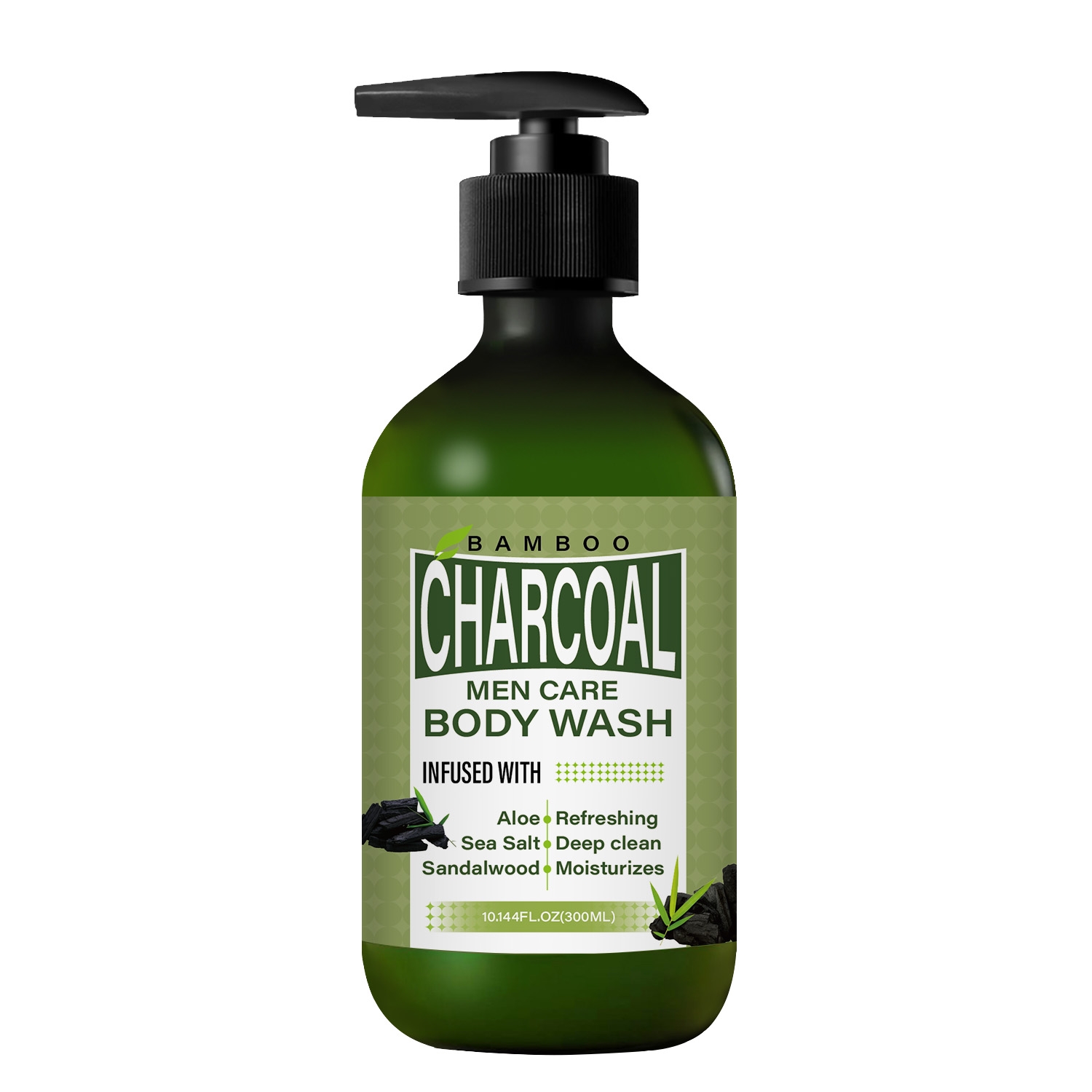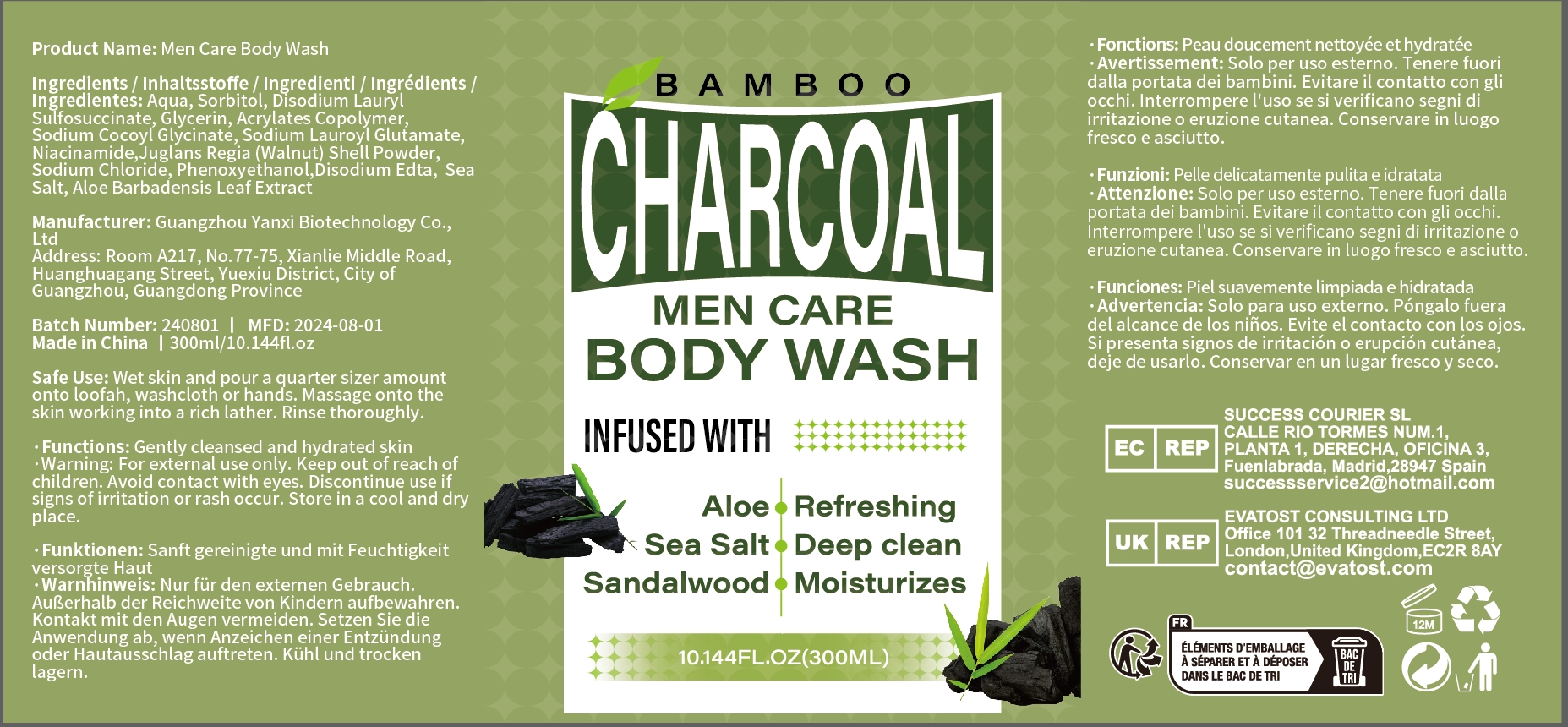 DRUG LABEL: Men Care Body Wash
NDC: 84025-296 | Form: CREAM
Manufacturer: Guangzhou Yanxi Biotechnology Co., Ltd
Category: otc | Type: HUMAN OTC DRUG LABEL
Date: 20241224

ACTIVE INGREDIENTS: GLYCERIN 5 mg/300 mL; SORBITOL 3 mg/300 mL
INACTIVE INGREDIENTS: WATER

DOSAGE AND ADMINISTRATION

Wet skin and pour a quarter sizer amount onto loofah, washcloth or hands. Massage onto the skin working into a rich lather. Rinse thoroughly

WARNINGS

Keep out of children

INACTIVE INGREDIENT

Aqua

INDICATIONS AND USAGE

For daily skin care

Keep out of children

PURPOSE

Gently cleansed and hydrated skin